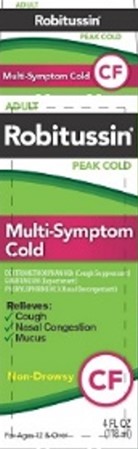 DRUG LABEL: Robitussin Peak Cold Multi-Symptom Cold
NDC: 0031-8742 | Form: LIQUID
Manufacturer: Haleon US Holdings LLC
Category: otc | Type: HUMAN OTC DRUG LABEL
Date: 20240406

ACTIVE INGREDIENTS: DEXTROMETHORPHAN HYDROBROMIDE 10 mg/5 mL; GUAIFENESIN 100 mg/5 mL; PHENYLEPHRINE HYDROCHLORIDE 5 mg/5 mL
INACTIVE INGREDIENTS: WATER; ANHYDROUS CITRIC ACID; FD&C RED NO. 40; GLYCERIN; MENTHOL, UNSPECIFIED FORM; PROPYLENE GLYCOL; SODIUM BENZOATE; SODIUM CITRATE, UNSPECIFIED FORM; SORBITOL; SUCRALOSE

Drug Facts

Active ingredients (in each 10 ml)

Dextromethorphan HBr, USP 20 mg

Guaifenesin, USP 200 mg

Phenylephrine HCl, USP 10 mg

Purposes

Cough suppressant

Expectorant

Nasal decongestant

Uses

- helps loosen phlegm (mucus) and thin bronchial secretions to drain bronchial tubes
- temporarily relieves these symptoms occurring with a cold:
  - nasal congestion
  - cough due to minor throat and bronchial irritation

Warnings

DO NOT USE

Do not useif you are now taking a prescription monoamine oxidase inhibitor (MAOI) (certain drugs for depression, psychiatric, or emotional conditions, or Parkinson's disease), or for 2 weeks after stopping the MAOI drug. If you do not know if your prescription drug contains an MAOI, ask a doctor or pharmacist before taking this product.

Ask a doctor before use if you have

- heart disease
- high blood pressure
- thyroid disease
- diabetes
- trouble urinating due to an enlarged prostate gland
- cough that occurs with too much phlegm (mucus)
- cough that lasts or is chronic such as occurs with smoking, asthma, chronic bronchitis or emphysema

Ask a doctor or pharmacist before use if you aretaking any other oral nasal decongestant or stimulant.

When using this product do not use more than directed.

Stop use and ask a doctor if

- you get nervous, dizzy, or sleepless
- symptoms do not get better within 7 days or are accompanied by fever
- cough lasts more than 7 days, comes back, or is accompanied by fever, rash, or persistent headache. These could be signs of a serious condition.

PREGNANCY OR BREAST FEEDING

If pregnant or breast-feeding,ask a health professional before use.

Keep out of reach of children.In case of overdose, get medical help or contact a Poison Control Center right away.

Directions

- do not take more than 6 doses in any 24-hour period
- measure only with dosing cup provided
- keep dosing cup with product
- ml = milliliter
- this adult product is not intended for use in children under 12 years of age

age | dose
adults and children 12 years and over | 10 ml every 4 hours
children under 12 years | do not use

Other information

- each 10 ml contains:sodium 6 mg
- store at 20-25°C (68-77°F). Do not refrigerate.

Inactive ingredients

anhydrous citric acid, FD&C red no. 40, glycerin, menthol, natural & artificial flavor, propylene glycol, purified water, sodium benzoate, sodium citrate, sorbitol solution, sucralose

Questions or comments?

call weekdays from 9 AM to 5 PM EST at 1-800-762-4675

For most recent product information,
visit www.robitussin.com

Distributed by:
Pfizer, Madison, NJ 07940 USA

PRINCIPAL DISPLAY PANEL

ADULT

Robitussin®

PEAK COLD

Multi-Symptom
Cold

DEXTROMETHORPHAN HBr (Cough Suppressant)
GUAIFENESIN (Expectorant)
PHENYLEPHRINE HCl (Nasal Decongestant)

Relieves:

- Cough
- Nasal Congestion
- Mucus

Non-Drowsy CF

For Ages 12 & Over

4 FL OZ
(118 ml)